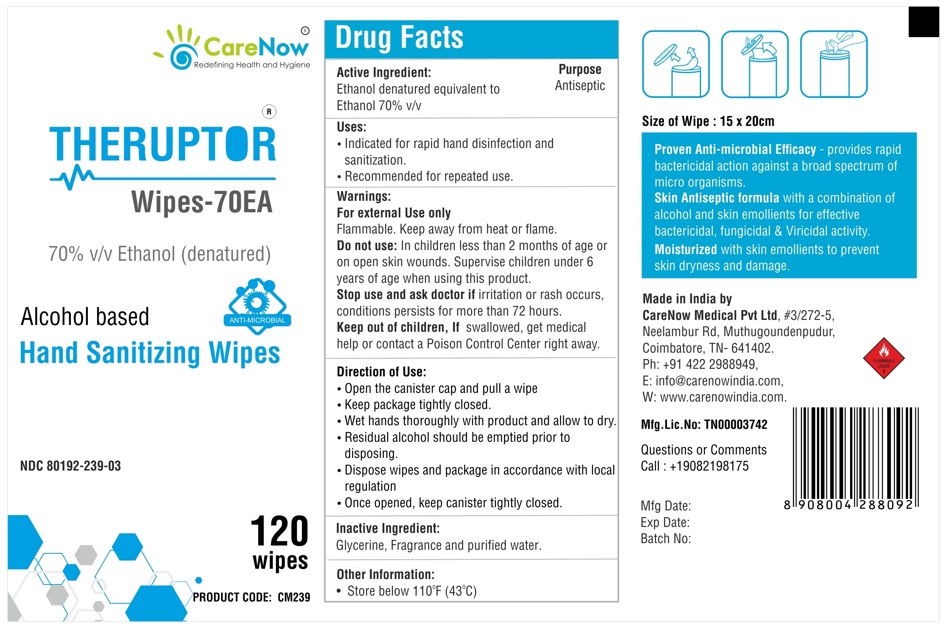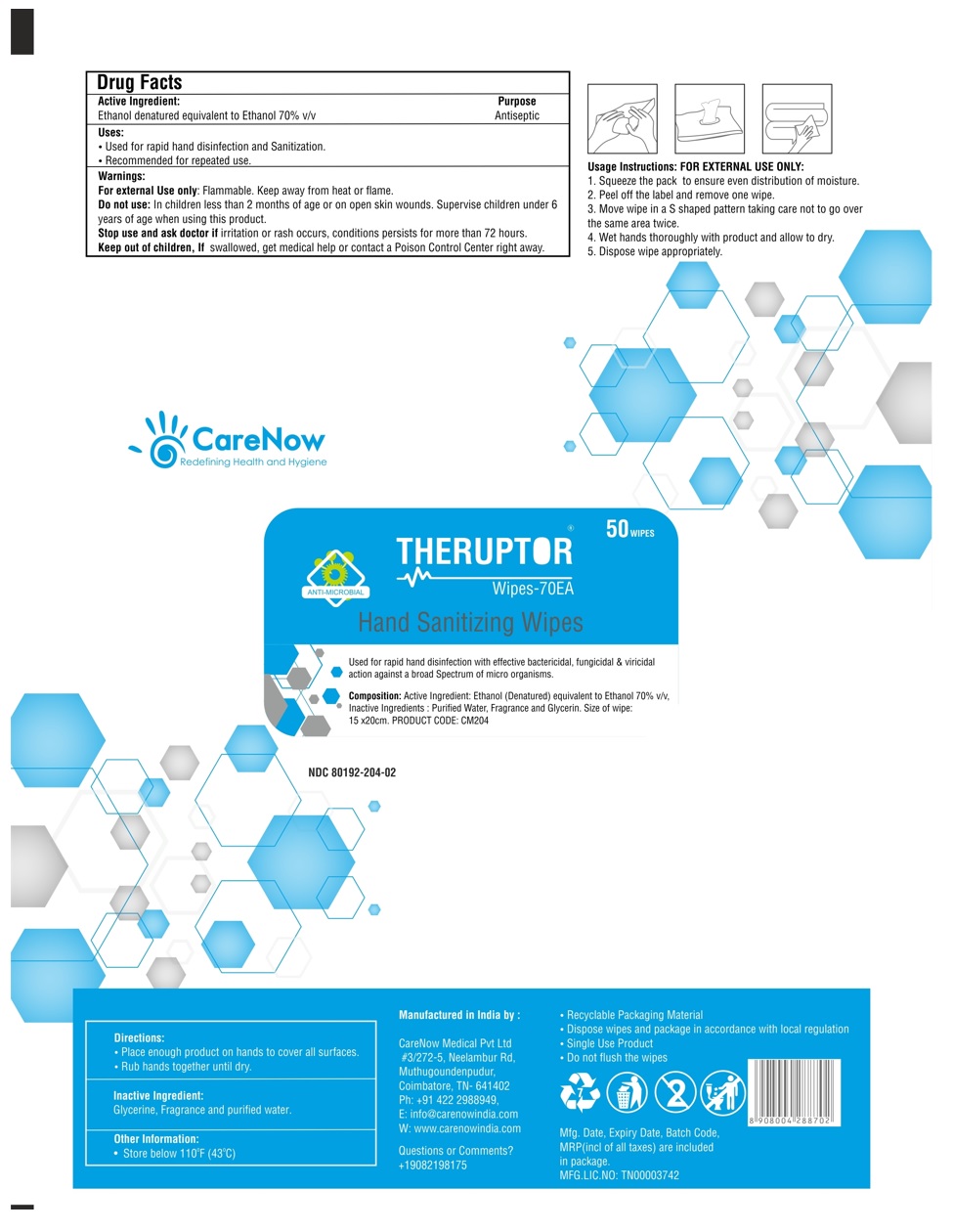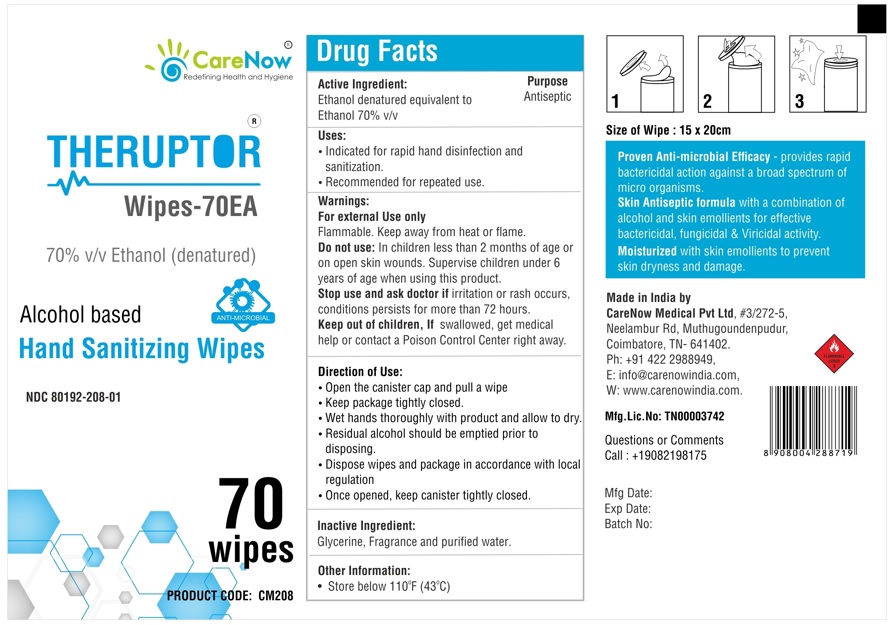 DRUG LABEL: THERUPTOR
NDC: 80192-208 | Form: CLOTH
Manufacturer: CareNow Medical Pvt Ltd
Category: otc | Type: HUMAN OTC DRUG LABEL
Date: 20220526

ACTIVE INGREDIENTS: ALCOHOL 70 mL/100 mL
INACTIVE INGREDIENTS: GLYCERIN; WATER

THERUPTOR®
Wipes-70EA

70% v/v Ethanol (denatured)

Alcohol based
Hand Sanitizing Wipes

Active Ingredient:

Ethanol denatured equivalent to Ethanol 70% v/v

Purpose

Antiseptic

Uses:

- Indicated for rapid hand disinfection and sanitization.
- Recommended for repeated use.

Warnings:

For external Use only
Flammable. Keep away from heat or flame.

Do not use: In children less than 2 months of age or on open skin wounds. Supervise children under 6 years of age when using this product.

Stop use and ask doctor if irritation or rash occurs, conditions persists for more than 72 hours.

KEEP OUT OF REACH OF CHILDREN

Keep out of children, If swallowed, get medical help or contact a Poison Control Center right away.

Direction of Use:

- Open the canister cap and pull a wipe
- Keep package tightly closed.
- Wet hands thoroughly with product and allow to dry.
- Residual alcohol should be emptied prior to disposing.
- Dispose wipes and package in accordance with local regulation
- Once opened, keep canister tightly closed.

Inactive Ingredient:

Glycerine, Fragrance and purified water.

Size of Wipe : 15 x 20cm

Other Information:

- Store below 110°F (43°C)

Proven Anti-microbial Efficacy - provides rapid bactericidal action against a broad spectrum of micro organisms.

Skin Antiseptic formula with a combination of alcohol and skin emollients for effective bactericidal, fungicidal & Viricidal activity.

Moisturized with skin emollients to prevent skin dryness and damage.

Made in India by
CareNow Medical Pvt Ltd, #3/272-5,
Neelambur Rd, Muthugoundenpudur,
Coimbatore, TN- 641402
Ph: +91 422 2988949,
E: info@carenowindia.com,
W: www.carenowindia.com

Mfg.Lic.No: TN00003742

Questions or Comments
Call : + 19082198175

Package Label - Principal Display Panel

NDC 80192-208-01

THERUPTOR® Wipes-70EA - 70 wipes

NDC 80192-204-02

THERUPTOR® Wipes-70EA - 50 wipes

NDC 80192-239-03

THERUPTOR® Wipes-70EA - 120 wipes